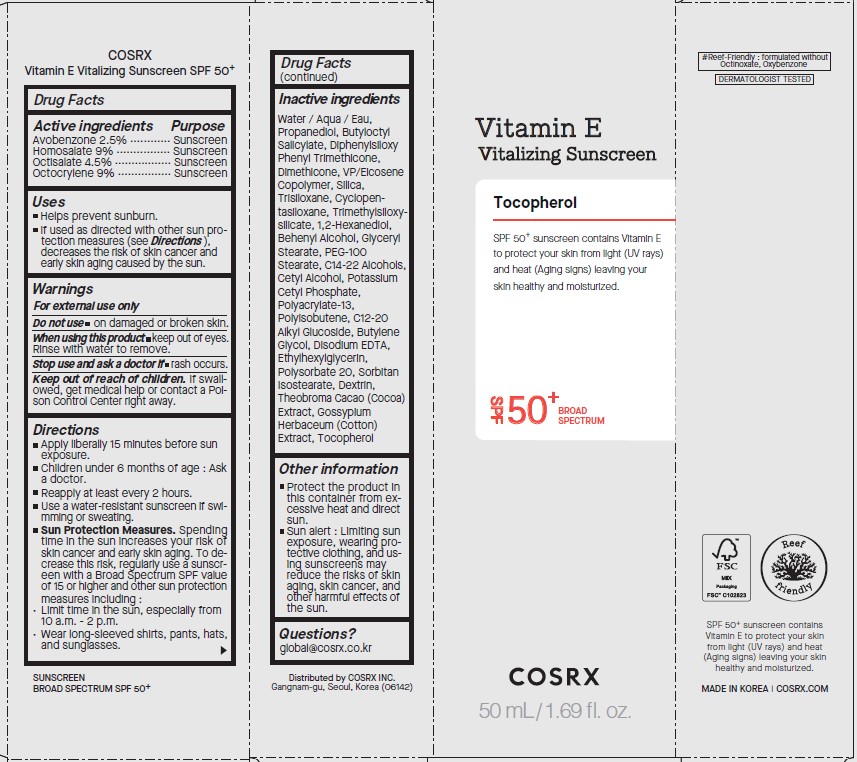 DRUG LABEL: COSRX
NDC: 70319-220 | Form: LOTION
Manufacturer: COSRX inc.
Category: otc | Type: HUMAN OTC DRUG LABEL
Date: 20251201

ACTIVE INGREDIENTS: AVOBENZONE 1.25 mg/50 mL; OCTOCRYLENE 2.25 mg/50 mL; HOMOSALATE 4.5 mg/50 mL; OCTISALATE 4.5 mg/50 mL
INACTIVE INGREDIENTS: 1,3-PROPANEDIOL BIS(4-AMINOBENZOATE); VINYLPYRROLIDONE/EICOSENE COPOLYMER; 1,2-HEXANEDIOL; DOCOSANOL; GLYCERYL MONOSTEARATE; C14-22 ALCOHOLS; SILICON DIOXIDE; TRISILOXANE; CYCLOMETHICONE 5; TRIMETHYLSILOXYSILICATE (M/Q 1.0-1.2); PEG-100 STEARATE; CETYL ALCOHOL; CETETH-18; BUTYLENE GLYCOL; DIPHENYLSILOXY PHENYL TRIMETHICONE; DIMETHICONE; ECHINACEA PURPUREA FLOWERING TOP WATER; ANHYDROUS DEXTROSE; POLYISOBUTYLENE (45000 MW); EDETATE DISODIUM; ETHYLHEXYLGLYCERIN; POLYSORBATE 20; SORBITAN ISOSTEARATE; COCOA; LEVANT COTTON SEED; .ALPHA.-TOCOPHEROL, DL-; POTASSIUM CETYL PHOSPHATE; C12-20 ALKYL GLUCOSIDE

ACTIVE INGREDIENT

Avobenzone 2.5%

Homosalate 9.0%

Octisalate 4.5%

Octocrylene 9.0%

PURPOSE

Sunscreen

WHEN USING

Helps prevent sunburn.
If used as directed with other sun protection measures (see Directions), decreases the risk of skin cancer and early skin aging caused by the sun.

WARNINGS

For external use only

Do not use on damanged or broken skin.

When using this product keep out of eyes. Rinse with water to remove.

Stop use and ask a doctor if rash occurs.

KEEP OUT OF REACH OF CHILDREN

If swallowed, get medical help or contact a Poison Control Center right away.

DESCRIPTION

Apply liberally 15 minutes before sun exposure
Children under 6 months of age : Ask a doctor.
Reapply at least every 2 hours.
Use a water-resistant sunscreen if swimming or sweating.
Sun Protection Measures. Spending time in the sun increases your risk of skin cancer and early skin aging. To decrease this risk, regularly use a sunscreen with a Broad Spectrum SPF value of 15 or higher and other sun protection measures including :

Limit time in the sun, especially from 10 a.m. - 2 p.m.

Wear long-sleeved shirts, pants, hats, and sunglasses.

OTHER SAFETY INFORMATION

Protect the product in this container from excessive heat and direct sun.
Sun alert : Limiting sun exposure, wearing protective clothing, and using sunscreens may reduce the risks of skin aging, skin cancer, and other harmful effects of the sun.

INACTIVE INGREDIENT

Water / Aqua / Eau, Propanediol, Butyloctyl salicylate, Diphenylsiloxy phenyl trimethicone, Dimethicone, VP/Eicosene copolymer, Silica, Trisiloxane, Cyclopentasiloxane, Trimethylsiloxysilicate, 1,2-Hexanediol, Behenyl alcohol, Glyceryl stearate, PEG-100 stearate, C14-22 alcohols, Cetyl alcohol, Potassium cetyl phosphate, Polyacrylate-13, Polyisobutene, Fragrance / Parfum, C12-20 Alkyl glucoside, Butylene glycol, Disodium EDTA, Ethylhexylglycerin, Polysorbate 20, Sorbitan isostearate, Dextrin, Theobroma cacao (cocoa) extract, Gossypium herbaceum (cotton) extract, Glucose, Tocopherol

QUESTIONS

global@cosrx.co.kr

PACKAGE LABEL

Vitamin E

Vitalizing Sunscreen

Tocopherol

SPF 50+ sunscreen contains Vitamin E

to protect your skin from light (UV rays)

and heat (Aging signs) leaving your

skin healthy and moisturized.

SPF50+ BROAD SPECTRUM

50mL /1.69 fl. oz.

COSRX